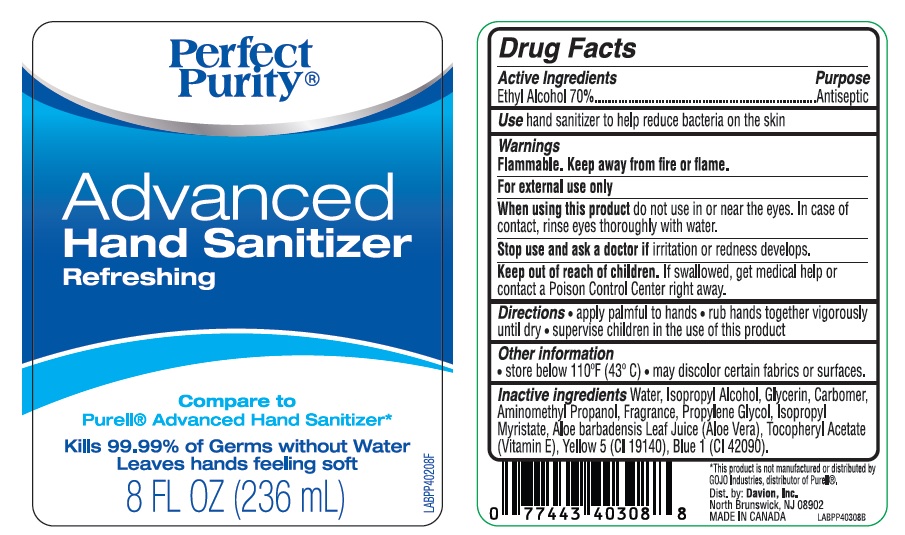 DRUG LABEL: Perfect Purity Advanced Hand Sanitizer Refreshing
NDC: 42669-002 | Form: SOLUTION
Manufacturer: Davion, Inc
Category: otc | Type: HUMAN OTC DRUG LABEL
Date: 20131218

ACTIVE INGREDIENTS: ALCOHOL 0.7 mL/1 mL
INACTIVE INGREDIENTS: WATER; ISOPROPYL ALCOHOL; GLYCERIN; CARBOMER INTERPOLYMER TYPE A (ALLYL SUCROSE CROSSLINKED); AMINOMETHYLPROPANOL; PROPYLENE GLYCOL; ISOPROPYL MYRISTATE; ALOE VERA LEAF; .ALPHA.-TOCOPHEROL ACETATE; FD&C YELLOW NO. 5; FD&C BLUE NO. 1

Advanced Hand Sanitizer

Drug Facts

Active Ingredients

Ethyl Alcohol 70%

Purpose

Antiseptic

Use

hand sanitizer to help reduce bacteria on the skin

Warnings

Flammable. Keep away from fire or flame.
For external use only.

When using this product do not use in or near the eyes. In case of contact, rinse eyes thoroughly with water.

Stop use and ask a doctor if irritation or redness develops.

Keep out of reach of children. If swallowed, get medical help or contact a Poison Control Center right away.

Directions

- apply palmful to hands
- rub hands together vigorously until dry
- supervise children in the use of this product

Other information

- store below 110°F (43°C)
- may discolor certain fabrics or surfaces.

Inactive ingredients

Water, Isopropyl Alcohol, Glycerin, Carbomer, Aminomethyl Propanol, Fragrance, Propylene Glycol, Isopropyl Myristate, Aloe barbadensis Leaf Juice (Aloe Vera), Tocopheryl Acetate (Vitamin E),Yellow 5 (CI 19140), Blue 1 (CI 42090).

* This product is not manufactured or distributed by GOJO Industries, distributor of Purell®

Dist. by: Davion, Inc.
North Brunswick, NJ 08902
MADE IN CANADA

Package Label

Perfect Purity®
Advanced
Hand Sanitizer
Refreshing

Compare to
Purell® Advanced Hand Sanitizer*

Kills 99.99% of Germs without Water
Leaves hands feeling soft

8 FL OZ (236 mL)